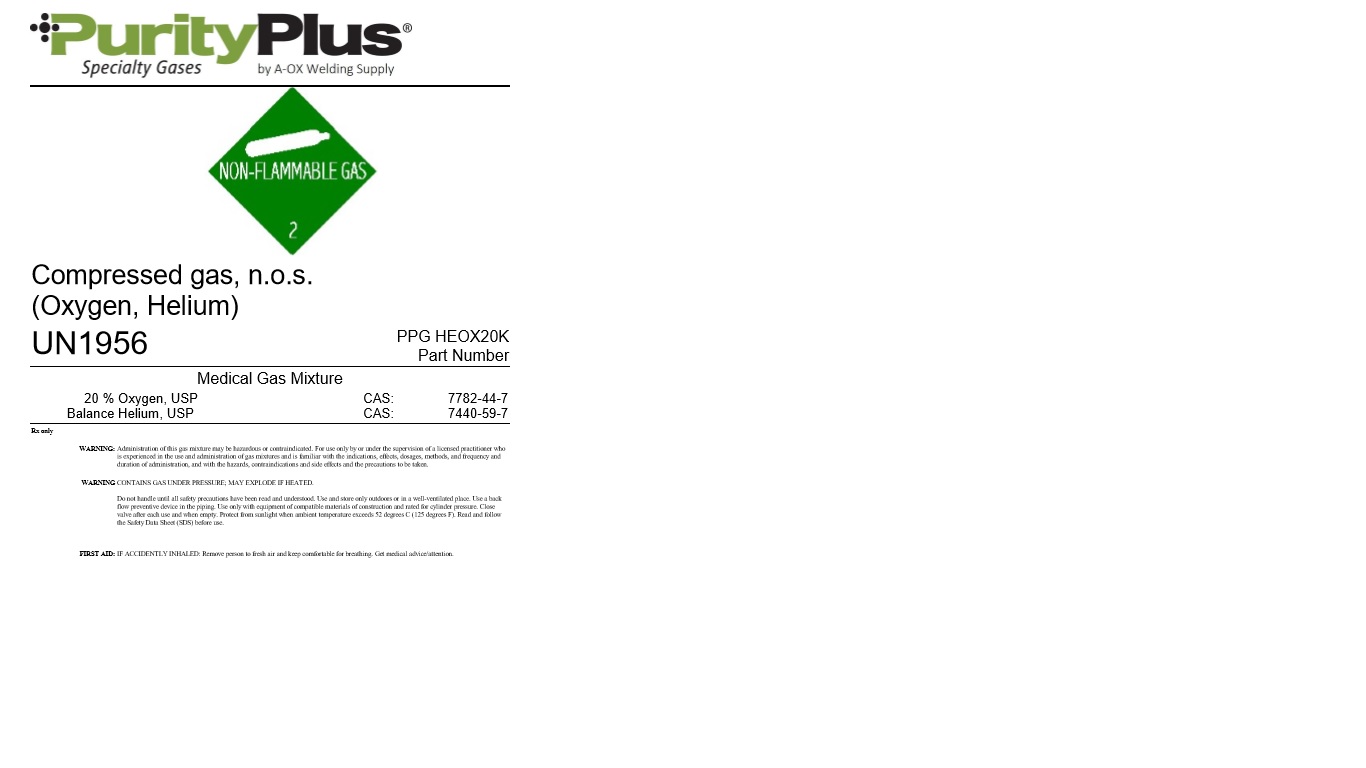 DRUG LABEL: Heliox
NDC: 10297-080 | Form: GAS
Manufacturer: A-OX Welding Supply, LLC
Category: prescription | Type: HUMAN PRESCRIPTION DRUG LABEL
Date: 20251023

ACTIVE INGREDIENTS: OXYGEN 200 mL/1 L
INACTIVE INGREDIENTS: HELIUM 800 mL/1 L

Heliox 20/80

PACKAGE LABEL

PurityPlus Specialty Gases by A-OX Welding Supply

Compressed gas, n.o.s. (Oxygen, Helium)

UN1956

PPG HEOX20K Part Number

Medical Gas Mixture

20 Percent Oxygen, USP CAS: 7782-44-7

Balance Helium, USP CAS: 7440-59-7

Rx only

WARNING: Administration of this gas mixture may be hazardous or contraindicated. For use only by or under the supervision of a licensed practitioner who is experienced in the use and administration of gas mixtures and is familiar with the indications, effects, dosages, methods, and frequency and duration of administration, and with the hazards, contraindications and side effects and the precautions to be taken.

WARNING CONTAINS GAS UNDER PRESSURE; MAY EXPLODE IF HEATED.

Do not handle until all safety precautions have been read and understood. Use and store only outdoors or in a well-ventilated place. Use a back flow preventive device in the piping. Use only with equipment of compatible materials of construction and rated for cylinder pressure. Close valve after each use and when empty. Protect from sunlight when ambient temperature exceeds 52 degrees C (125 degrees F). Read and follow the Safety Data Sheet (SDS) before use.

FIRST AID: IF ACCIDENTLY INHALED: Remove person to fresh air and keep comfortable for breathing. Get medical advice/attention.

DO NOT REMOVE THIS PRODUCT LABEL

For Medical Use Only.

Ver. 3.90

A-OX Welding Supply Co.

101 N. Harlem Ave.

Sioux Falls, SD 57104

605.336.1125